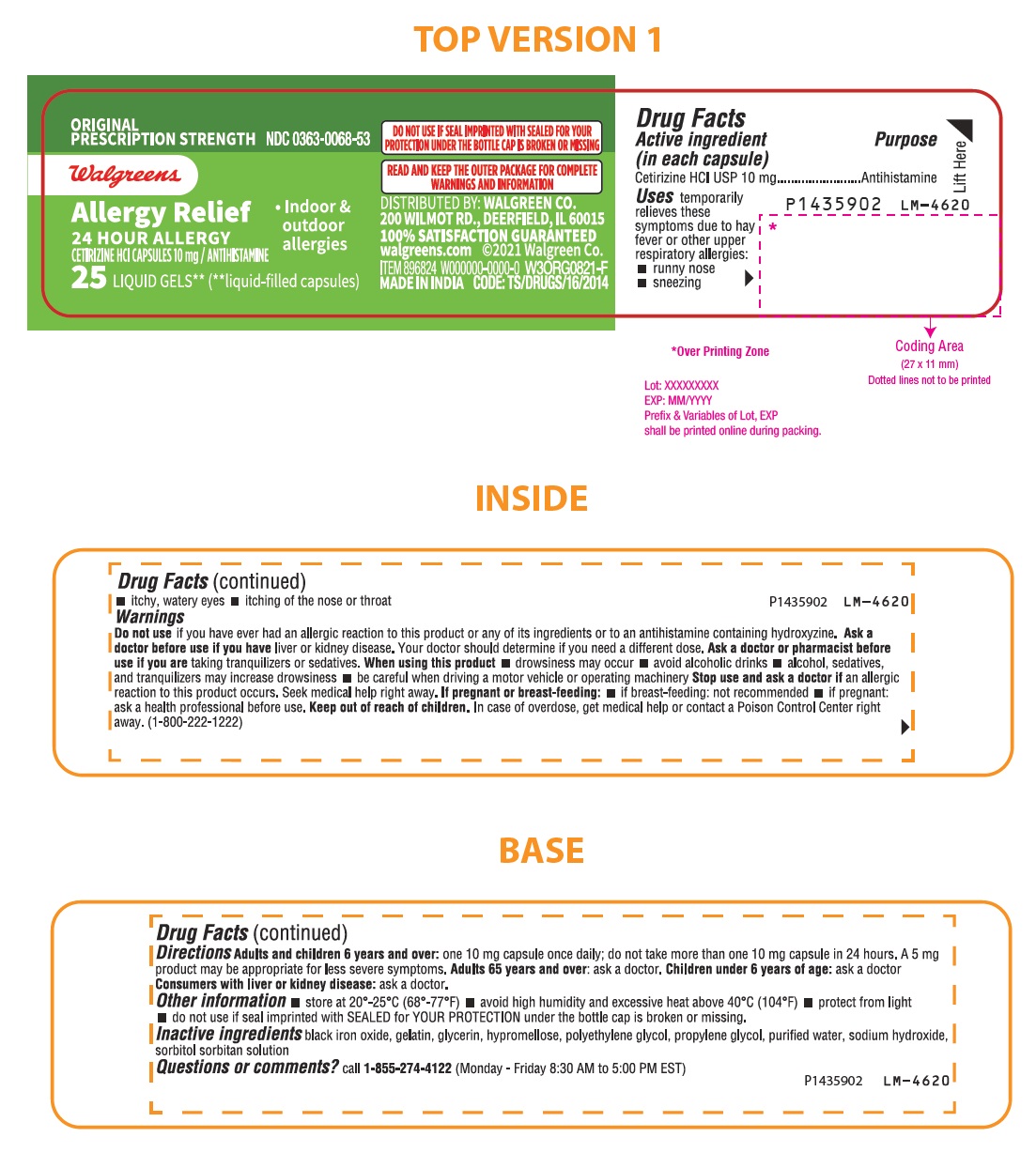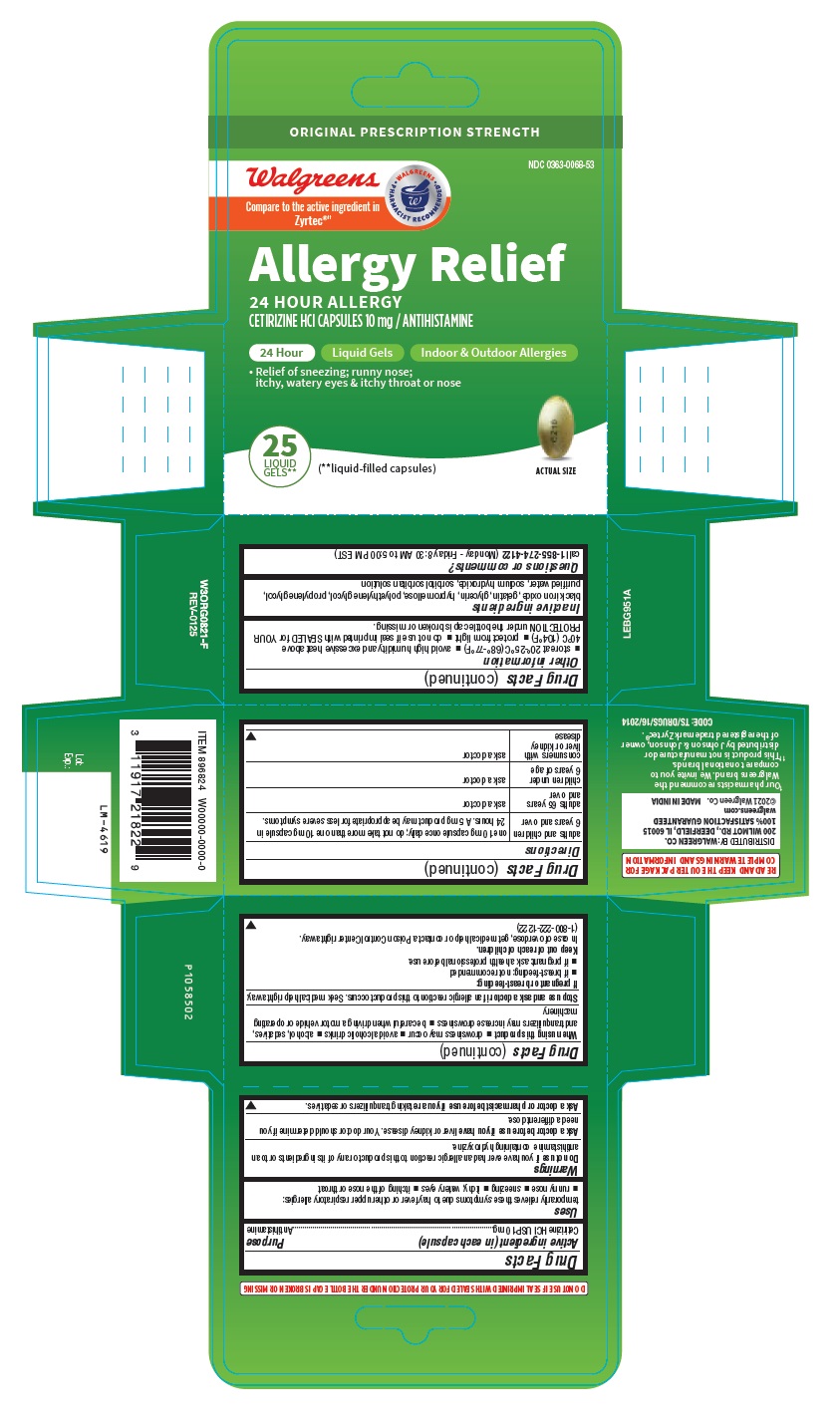 DRUG LABEL: Cetirizine Hydrochloride (Allergy)
NDC: 0363-0068 | Form: CAPSULE
Manufacturer: WALGREEN CO.
Category: otc | Type: Human OTC Drug Label
Date: 20250405

ACTIVE INGREDIENTS: CETIRIZINE HYDROCHLORIDE 10 mg/1 1
INACTIVE INGREDIENTS: FERROSOFERRIC OXIDE; GELATIN, UNSPECIFIED; GLYCERIN; HYPROMELLOSE 2910 (6 MPA.S); POLYETHYLENE GLYCOL 400; PROPYLENE GLYCOL; WATER; SODIUM HYDROXIDE; SORBITOL

Cetirizine HCl Capsules 10 mg (Allergy)
Drug Facts

Active ingredient (in each capsule)

Cetirizine HCI USP 10 mg

Purpose

Antihistamine

Uses

temporarily relieves these symptoms due to hay fever or other upper respiratory allergies:

- runny nose
- sneezing
- itchy, watery eyes
- itching of the nose or throat

Warnings

Do not use if you have ever had an allergic reaction to this product or any of its ingredients or to an antihistamine containing hydroxyzine.

Ask a doctor before use if you have liver or kidney disease. Your doctor should determine if you need a different dose.

Ask a doctor or pharmacist before use if you are taking tranquilizers or sedatives.

When using this product

- drowsiness may occur
- avoid alcoholic drinks
- alcohol, sedatives, and tranquilizers may increase drowsiness
- be careful when driving a motor vehicle or operating machinery

Stop use and ask a doctor if

an allergic reaction to this product occurs. Seek medical help right away.

If pregnant or breast-feeding:

- If breast-feeding: not recommended
- if pregnant: ask a health professional before use.

Keep out of reach of children.

In case of overdose, get medical help or contact a Poison Control Center right away. (1-800-222-1222)

Directions

adults and children 6 years and over | one 10 mg capsule once daily; do not take more than one 10 mg capsule in 24 hours. A 5 mg product may be appropriate for less severe symptoms.
adults 65 years and over | ask a doctor
children under 6 years of age | ask a doctor
consumers with liver or kidney disease | ask a doctor

Other information

- store at 20°-25°C (68°-77°F)
- avoid high humidity and excessive heat above 40°C (104°F)
- protect from light
- do not use if seal imprinted with SEALED for YOUR PROTECTION under the bottle cap is broken or missing.

Inactive ingredients

black iron oxide, gelatin, glycerin, hypromellose, polyethylene glycol, propylene glycol, purified water, sodium hydroxide, sorbitol sorbitan solution

Questions or comments?

call 1-855-274-4122 (Monday - Friday 8:30 AM to 5:00 PM EST)

DISTRIBUTED BY: WALGREEN CO.
200 WILMOT RD., DEERFIELD, IL 60015
100% SATISFACTION GUARANTEED
Walgreens.com ©2021 Walgreen Co.

PACKAGE LABEL-PRINCIPAL DISPLAY PANEL - 10 mg (25's Capsule Container Label)

ORIGINAL
PRESCRIPTION STRENGTH NDC 0363-0068-53
walgreens
Allergy Relief
24 HOUR ALLERGY
CETIRIZINE HCl CAPSULES 10 mg / ANTIHISTAMINE
• Indoor & outdoor allergies
25 LIQUID GELS**
(**LIQUID-FILLED CAPSULES)

PACKAGE LABEL-PRINCIPAL DISPLAY PANEL -10 mg (25's Capsule Container Carton Label)

ORIGINAL
PRESCRIPTION STRENGTH

NDC 0363-0068-53
walgreens
Compare to the active ingredient in
Zyrtec®††
Allergy Relief
24 HOUR ALLERGY
CETIRIZINE HCl CAPSULES 10 mg / ANTIHISTAMINE
24 Hour Liquid Gels Indoor & Outdoor Allergies

• Relief of sneezing; runny nose;

itchy, watery eyes & itchy throat or nose

CZ10
ACTUAL SIZE

25

LIQUID

GELS** (**liquid-filled capsules)